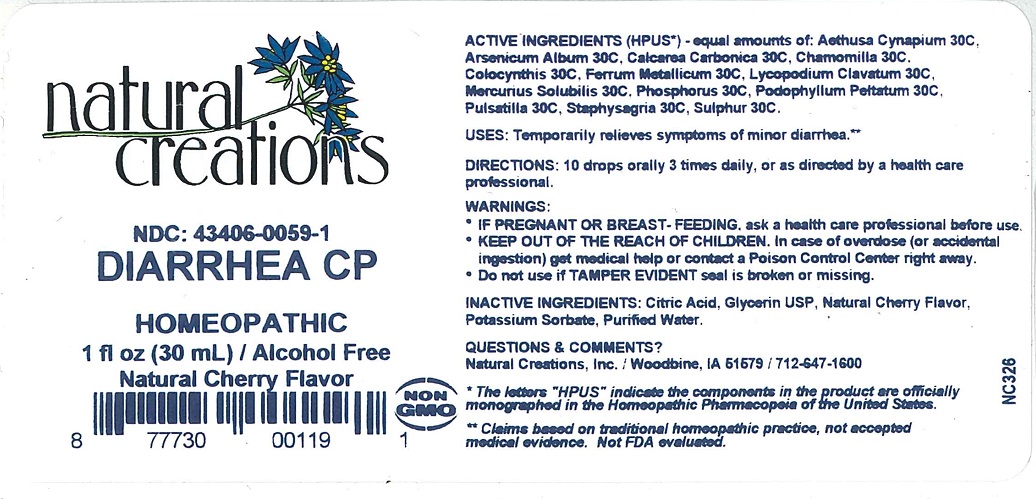 DRUG LABEL: DIARRHEA CP
NDC: 43406-0059 | Form: LIQUID
Manufacturer: Natural Creations, Inc.
Category: homeopathic | Type: HUMAN OTC DRUG LABEL
Date: 20251210

ACTIVE INGREDIENTS: AETHUSA CYNAPIUM 30 [hp_C]/1 mL; ARSENIC TRIOXIDE 30 [hp_C]/1 mL; OYSTER SHELL CALCIUM CARBONATE, CRUDE 30 [hp_C]/1 mL; MATRICARIA RECUTITA 30 [hp_C]/1 mL; CITRULLUS COLOCYNTHIS FRUIT PULP 30 [hp_C]/1 mL; IRON 30 [hp_C]/1 mL; LYCOPODIUM CLAVATUM SPORE 30 [hp_C]/1 mL; MERCURIUS SOLUBILIS 30 [hp_C]/1 mL; PHOSPHORUS 30 [hp_C]/1 mL; PODOPHYLLUM 30 [hp_C]/1 mL; ANEMONE PULSATILLA 30 [hp_C]/1 mL; DELPHINIUM STAPHISAGRIA SEED 30 [hp_C]/1 mL; SULFUR 30 [hp_C]/1 mL
INACTIVE INGREDIENTS: WATER; POTASSIUM SORBATE; CITRIC ACID ACETATE; GLYCERIN

DIARRHEA CP

ACTIVE INGREDIENT

Active Ingredients (HPUS*) - equal amounts of: Aethusa Cynapium 30C, Arsenicum Album 30C, Calcarea Carbonica 30C, Chamomilla 30C, Colocynthis 30C, Ferrum Metallicum 30C, Lycopodium Clavatum 30C, Mercurius Solubilis 30C, Phosphorus 30C, Podophyllum Peltatum 30C, Pulsatilla 30C, Staphysagria 30C, Sulphur 30C.

PURPOSE

Uses: Temporarily relieves symptoms of minor diarrhea.**

INDICATIONS AND USAGE

Uses: Temporarily relieves symptoms of minor diarrhea.**

DOSAGE AND ADMINISTRATION

Directions: 10 drops orally 3 times daily, or as directed by a health care professional.

KEEP OUT OF REACH OF CHILDREN

KEEP OUT OF THE REACH OF CHILDREN. In case of overdose (or accidental ingestion) get

medical help or contact a Poison Control Center right away.

WARNINGS:

- Consult a physician for use in children under 12 years of age.
- IF PREGNANT OR BREAST-FEEDING, ask a health care professional before use.
- KEEP OUT OF THE REACH OF CHILDREN. In case of overdose (or accidental ingestion) get medical help or contact a Poison Control Center right away.
- Do not use if TAMPER EVIDENT seal is broken or missing.

INACTIVE INGREDIENT

Inactive Ingredients: Citric Acid, Glycerin USP, Natural Cherry Flavor, Potassium Sorbate, Purified Water.

Questions & Comments?

Natural Creations, Inc. / Woodbine, IA 51579 / 712-647-1600

REFERENCES

*The letters “HPUS” indicate the components in the product are officially monographed in the Homeopathic Pharmacopeia of the United States.

**Claims based on traditional homeopathic practice, not accepted medical evidence. Not FDA evaluated.

PACKAGE LABEL

NDC: 43406-0059-1

DIARRHEA CP

HOMEOPATHIC

1 fl oz (30 mL) / Alcohol Free

Natural Cherry Flavor

UPC: 877730001191